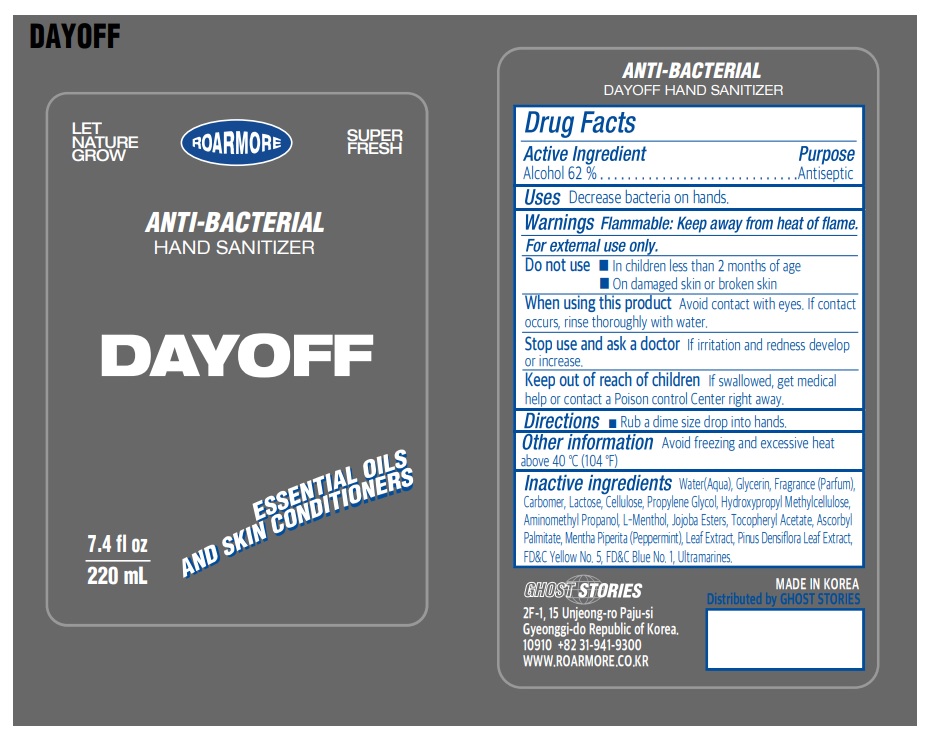 DRUG LABEL: ANTI-BACTERIAL DAYOFF HAND SANITIZER
NDC: 82697-221 | Form: GEL
Manufacturer: GHOST STORIES
Category: otc | Type: HUMAN OTC DRUG LABEL
Date: 20220413

ACTIVE INGREDIENTS: ALCOHOL 136.4 mL/220 mL
INACTIVE INGREDIENTS: FD&C BLUE NO. 1; LACTOSE, UNSPECIFIED FORM; HYDROGENATED JOJOBA OIL, RANDOMIZED; MENTHA PIPERITA LEAF; FD&C YELLOW NO. 5; ULTRAMARINE BLUE; WATER; GLYCERIN; CARBOMER HOMOPOLYMER, UNSPECIFIED TYPE; AMINOMETHYLPROPANOL; LEVOMENTHOL; ALPHA-TOCOPHEROL ACETATE; ASCORBYL PALMITATE; PINUS DENSIFLORA LEAF; POWDERED CELLULOSE; PROPYLENE GLYCOL; HYPROMELLOSE, UNSPECIFIED

82697-221-01 | ANTI-BACTERIAL DAYOFF HAND SANITIZER

Active ingredient

Alcohol 62%

Purpose

Antiseptic

Uses

Decrease bacteria on hands.

Warnings

Flammable: Keep away from heat of flame.

For external use only.

Do not use

- In children less than 2 months of age
- On damaged skin or broken skin

When using this product

Avoid contact with eyes. If contact occurs, rinse thoroughly with water.

Stop use and ask a doctor

If irritation and redness develop or increase.

Keep out of reach of children

If swallowed, get medical help or contact a Poison Control Cente right away.

Directions

- Rub a dime size drop into hands.

Other information

Avoid freezing and excessive heat above 40 °C (104 °F)

Inactive ingredients

Water(Aqua), Glycerin, Fragrance (Parfum), Carbomer, Lactose, Cellulose, Propylene Glycol, Hydroxypropyl Methylcellulose, Aminomethyl Propanol, L-Menthol, Jojoba Esters, Tocopheryl Acetate, Ascorbyl Palmitate, Mentha Piperita (Peppermint), Leaf Extract, Pinus Densiflora Leaf Extract, FD&C Yellow No. 5, FD&C Blue No. 1, Ultramarines.